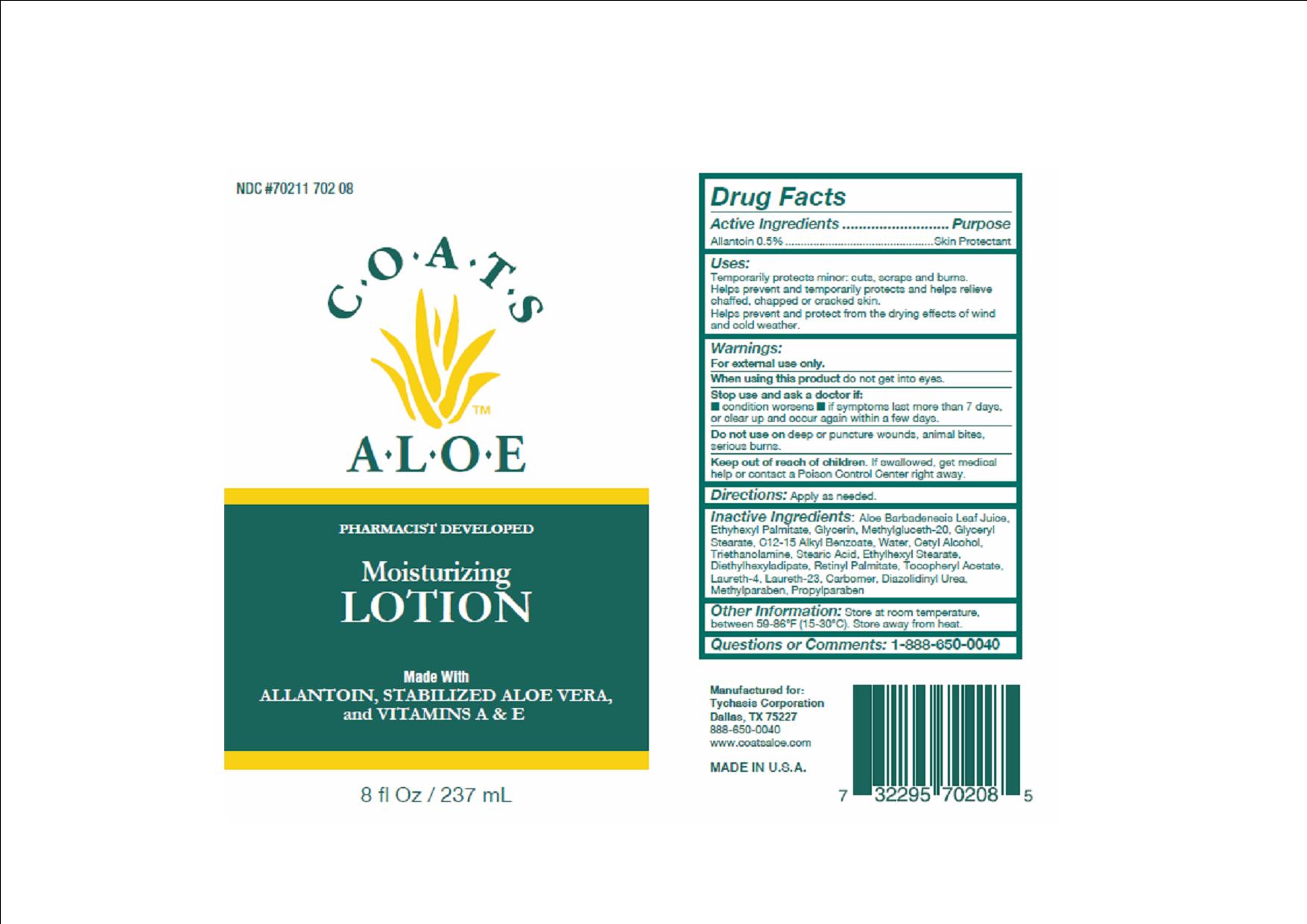 DRUG LABEL: COATS ALOE
NDC: 70211-702 | Form: LOTION
Manufacturer: TYCHASIS CORPORATION
Category: otc | Type: HUMAN OTC DRUG LABEL
Date: 20241028

ACTIVE INGREDIENTS: ALLANTOIN 0.5 g/100 mL
INACTIVE INGREDIENTS: ALOE VERA LEAF; ETHYLHEXYL PALMITATE; METHYL GLUCETH-20; ETHYLHEXYL STEARATE; GLYCERYL STEARATE SE; ALKYL (C12-15) BENZOATE; CETYL ALCOHOL; STEARIC ACID; DIETHYLHEXYL ADIPATE; VITAMIN A PALMITATE; TOCOPHEROL; LAURETH-4; LAURETH-23; DIAZOLIDINYL UREA; PROPYLPARABEN; WATER; METHYLPARABEN; BOROGLYCERIN

COATS ALOE LOTION

Active Ingredient:

Allantoin 0.5%

Purpose:

Skin Protectant.

Warnings:

For external use only.

Do not get into eyes.

Stop use if:

Stop use and ask a doctor if condition worsens, symptoms last more than 7 days, or clear up and occur again within a few days.

Uses:

Temporarily protects minor:

- cuts
- scapes
- burns

Helps prevent and temporarily protects and helps relieve chaffed, chapped, or cracked skin.

Helps prevent and protect from the drying effects of wind and cold weather.

Caution:

Do not use on deep puncture wounds, animal bites, serious burns.

Keep out of reach of children:

If swallowed get medical help or contact a poison control center right away.

Directions:

Apply as needed.

Inactive Ingredients:

aloe barbanesis leaf juice, ethylhexyl palmitate, glycerin, methylgluceth-20, glyceryl stearate, C12-15 alkyl benzoate, water, cetyl alcohol, triethanolomine, stearic acid, ethylhexyl stearate, diethylhexyl adipate, retinyl palmitate, tocopheryl acetate, laureth-4, laureth-23, carbomer, diazolidinyl urea, methylparaben, propylparaben

Questions:

Toll free 888-650-0040